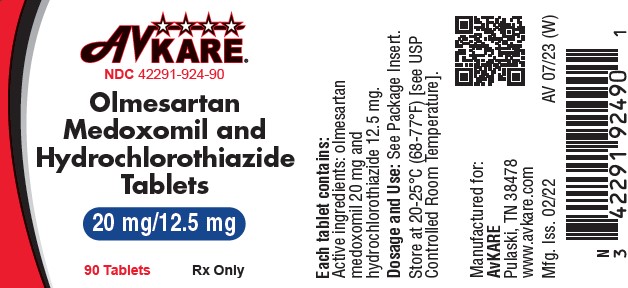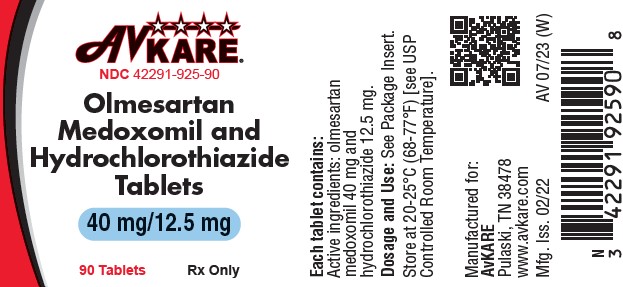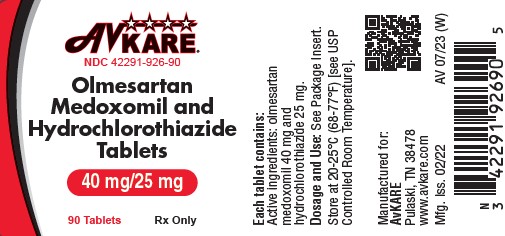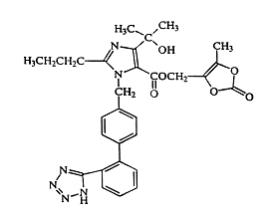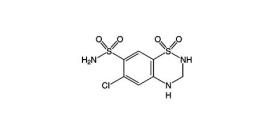 DRUG LABEL: olmesartan medoxomil-hydrochlorothiazide
NDC: 42291-924 | Form: TABLET, FILM COATED
Manufacturer: AvKARE
Category: prescription | Type: HUMAN PRESCRIPTION DRUG LABEL
Date: 20260119

ACTIVE INGREDIENTS: OLMESARTAN MEDOXOMIL 20 mg/1 1; HYDROCHLOROTHIAZIDE 12.5 mg/1 1
INACTIVE INGREDIENTS: HYDROXYPROPYL CELLULOSE (1600000 WAMW); HYPROMELLOSE, UNSPECIFIED; LACTOSE MONOHYDRATE; LOW-SUBSTITUTED HYDROXYPROPYL CELLULOSE, UNSPECIFIED; MAGNESIUM STEARATE; MICROCRYSTALLINE CELLULOSE; FERRIC OXIDE RED; TALC; TITANIUM DIOXIDE; FERRIC OXIDE YELLOW

HIGHLIGHTS OF PRESCRIBING INFORMATION

Olmesartan Medoxomil and Hydrochlorothiazide Tablets
Rx Only
These highlights do not include all the information needed to use Olmesartan Medoxomil and Hydrochlorothiazide safely and effectively. See full prescribing information for Olmesartan Medoxomil and Hydrochlorothiazide.
Initial U.S. Approval: 2003

WARNING: FETAL TOXICITY

See full prescribing information for complete boxed warning.

- When pregnancy is detected, discontinue olmesartan medoxomil and hydrochlorothiazide as soon as possible (5.1).
- Drugs that act directly on the renin-angiotensin system can cause injury and death to the developing fetus (5.1).

1 INDICATIONS AND USAGE

- Olmesartan medoxomil and hydrochlorothiazide is a combination of olmesartan, an angiotensin II receptor blocker and hydrochlorothiazide, a thiazide diuretic indicated for the treatment of hypertension, to lower blood pressure. Lowering blood pressure reduces the risk of fatal and nonfatal cardiovascular events, primarily strokes and myocardial infarctions. (1)

2 DOSAGE AND ADMINISTRATION

- Recommended starting dose in patients not adequately controlled with olmesartan monotherapy, 40/12.5 mg (2)
- Recommended starting dose in patients not adequately controlled with hydrochlorothiazide monotherapy, 20/12.5 mg (2)
- Adjust dose after 2 to 4 weeks, as needed, to a maximum of 40 mg / 25 mg olmesartan / hydrochlorothiazide (2)

3 DOSAGE FORMS AND STRENGTHS

Tablets: (olmesartan medoxomil and hydrochlorothiazide) 20/12.5 mg; 40/12.5 mg; 40/25 mg (3)

4 CONTRAINDICATIONS

- Hypersensitivity to any component of olmesartan medoxomil and hydrochlorothiazide (4)
- Anuria (4)
- Do not co-administer aliskiren with olmesartan medoxomil and hydrochlorothiazide in patients with diabetes. (4)

5 WARNINGS AND PRECAUTIONS

- Hypotension: Correct volume-depletion prior to administration. (5.2)
- Monitor renal function and potassium in susceptible patients (5.3)
- Observe for signs of fluid or electrolyte imbalance. (5.4)
- Acute angle-closure glaucoma (5.5)
- Sprue-like enteropathy has been reported. Consider discontinuation of olmesartan medoxomil and hydrochlorothiazide in cases where no other etiology is found (5.7)

6 ADVERSE REACTIONS

Most common adverse reactions (incidence ≥2%) are nausea, hyperuricemia, dizziness, and upper respiratory infection (6.1)

To report SUSPECTED ADVERSE REACTIONS, contact AvKARE at 1-855-361-3993 or FDA at 1-800-332-1088 or www.fda.gov/medwatch.

7 DRUG INTERACTIONS

- Lithium: Risk of lithium toxicity (7.2)
- Non-Steroidal Anti-Inflammatory Drugs (NSAIDs): Reduced diuretic, natriuretic and antihypotensive effects; increased risk of renal toxicity (7.3)
- Dual inhibition of the renin-angiotensin system: Increased risk of renal impairment, hypotension, and hyperkalemia (7.4)
- Colesevelam hydrochloride: Consider administering olmesartan at least 4 hours before colesevelam hydrochloride dose (7.5)
- Antidiabetic drugs: Dosage adjustment may be required (7.6)
- Cholestyramine and colestipol: Reduced absorption of thiazides (7.6)

8 USE IN SPECIFIC POPULATIONS

- Nursing mothers: Avoid use while nursing; discontinue either nursing or the drug (8.3).

FULL PRESCRIBING INFORMATION

WARNING: FETAL TOXICITY

- When pregnancy is detected, discontinue olmesartan medoxomil and hydrochlorothiazide as soon as possible [see Warnings and Precautions (5.1)].
- Drugs that act directly on the renin-angiotensin system can cause injury and death to the developing fetus [see Warnings and Precautions (5.1)].

1 INDICATIONS AND USAGE

Olmesartan medoxomil and hydrochlorothiazide is indicated for the treatment of hypertension, to lower blood pressure. Olmesartan medoxomil and hydrochlorothiazide is not indicated for the initial therapy of hypertension [see Dosage and Administration (2)].

Lowering blood pressure reduces the risk of fatal and nonfatal cardiovascular events, primarily strokes and myocardial infarctions. These benefits have been seen in controlled trials of antihypertensive drugs from a wide variety of pharmacologic classes including the class to which this drug principally belongs. There are no controlled trials demonstrating risk reduction with olmesartan medoxomil and hydrochlorothiazide.

Control of high blood pressure should be part of comprehensive cardiovascular risk management, including, as appropriate, lipid control, diabetes management, antithrombotic therapy, smoking cessation, exercise, and limited sodium intake. Many patients will require more than one drug to achieve blood pressure goals. For specific advice on goals and management, see published guidelines, such as those of the National High Blood Pressure Education Program’s Joint National Committee on Prevention, Detection, Evaluation, and Treatment of High Blood Pressure (JNC).

Numerous antihypertensive drugs, from a variety of pharmacologic classes and with different mechanisms of action, have been shown in randomized controlled trials to reduce cardiovascular morbidity and mortality, and it can be concluded that it is blood pressure reduction, and not some other pharmacologic property of the drugs, that is largely responsible for those benefits. The largest and most consistent cardiovascular outcome benefit has been a reduction in the risk of stroke, but reductions in myocardial infarction and cardiovascular mortality also have been seen regularly.

Elevated systolic or diastolic pressure causes increased cardiovascular risk, and the absolute risk increase per mmHg is greater at higher blood pressures, so that even modest reductions of severe hypertension can provide substantial benefit. Relative risk reduction from blood pressure reduction is similar across populations with varying absolute risk, so the absolute benefit is greater in patients who are at higher risk independent of their hypertension (for example, patients with diabetes or hyperlipidemia), and such patients would be expected to benefit from more aggressive treatment to a lower blood pressure goal.

Some antihypertensive drugs have smaller blood pressure effects (as monotherapy) in black patients, and many antihypertensive drugs have additional approved indications and effects (e.g., on angina, heart failure, or diabetic kidney disease). These considerations may guide selection of therapy.

Olmesartan medoxomil and hydrochlorothiazide may be used alone, or in combination with other antihypertensive drugs.

2 DOSAGE AND ADMINISTRATION

The recommended starting dose of olmesartan medoxomil and hydrochlorothiazide is 40/12.5 mg once daily in patients whose blood pressure is not adequately controlled with olmesartan monotherapy. Dose can be titrated up to 40 /25 mg if necessary.

The recommended starting dose of olmesartan medoxomil and hydrochlorothiazide is 20/12.5 mg once daily in patients whose blood pressure is not adequately controlled with HCT monotherapy or who experience dose-limiting adverse reactions with hydrochlorothiazide. Dose can be titrated up to 40 /25 mg if necessary.

Patients titrated to the individual components (olmesartan and hydrochlorothiazide) may instead receive the corresponding dose of olmesartan medoxomil and hydrochlorothiazide.

3 DOSAGE FORMS AND STRENGTHS

Olmesartan medoxomil and hydrochlorothiazide is supplied as film-coated, non-scored tablets:

- 20 mg/12.5 mg reddish-yellow, circular, debossed with Sankyo on one side and C22 on the other side
- 40 mg/12.5 mg reddish-yellow, oval, debossed with Sankyo on one side and C23 on the other side
- 40 mg/25 mg pink, oval, debossed with Sankyo on one side and C25 on the other side

4 CONTRAINDICATIONS

Olmesartan medoxomil and hydrochlorothiazide is contraindicated:

- In patients with hypersensitivity to any component of olmesartan medoxomil and hydrochlorothiazide [see Adverse Reactions (6.1,6.2)]
- In patients with anuria [see Warnings and Precautions (5.3) and Adverse Reactions (6.1)]
- For coadministration with aliskiren in patients with diabetes [see Drug Interactions (7.4)].

5 WARNINGS AND PRECAUTIONS

5.1 Fetal Toxicity

Pregnancy Category D

Use of drugs that act on the renin-angiotensin system during the second and third trimesters of pregnancy reduces fetal renal function and increases fetal and neonatal morbidity and death. Resulting oligohydramnios can be associated with fetal lung hypoplasia and skeletal deformations. Potential neonatal adverse effects include skull hypoplasia, anuria, hypotension, renal failure, and death. When pregnancy is detected, discontinue olmesartan medoxomil and hydrochlorothiazide as soon as possible [see Use in Specific Populations (8.1)].

Thiazides cross the placental barrier and appear in cord blood. Adverse reactions include fetal or neonatal jaundice and thrombocytopenia [see Use in Specific Populations (8.1)].

5.2 Hypotension in Volume or Salt-Depleted Patients

In patients with an activated renin-angiotensin system, such as volume- or salt-depleted patients (e.g.,those being treated with high doses of diuretics), symptomatic hypotension may occur after initiation of treatment with olmesartan medoxomil and hydrochlorothiazide. If hypotension does occur, the patient should be placed in the supine position and, if necessary, given an intravenous infusion of normal saline. When electrolyte and fluid imbalances have been corrected, olmesartan medoxomil and hydrochlorothiazide usually can be continued without difficulty. A transient hypotensive response is not a contraindication to further treatment.

5.3 Impaired Renal Function

Changes in renal function including acute renal failure can be caused by drugs that inhibit the renin-angiotensin system and by diuretics. Patients whose renal function may depend in part on the activity of the renin-angiotensin system (e.g., patients with renal artery stenosis, chronic kidney disease, severe congestive heart failure, or volume depletion) may be at particular risk of developing acute renal failure on olmesartan medoxomil and hydrochlorothiazide. Monitor renal function periodically in these patients. Consider withholding or discontinuing therapy in patients who develop a clinically significant decrease in renal function on olmesartan medoxomil and hydrochlorothiazide [see Drug Interactions (7)].

5.4 Hypersensitivity Reactions

Hypersensitivity reactions to hydrochlorothiazide may occur in patients with or without a history of allergy or bronchial asthma, but are more likely in patients with such a history.

5.5 Electrolyte and Metabolic Imbalances

Olmesartan medoxomil and hydrochlorothiazide contains hydrochlorothiazide which can cause hypokalemia and hyponatremia. Hypomagnesemia can result in hypokalemia which may be difficult to treat despite potassium repletion.Olmesartan medoxomil and hydrochlorothiazide also contains olmesartan, a drug that inhibits the renin-angiotensin system (RAS). Drugs that inhibit the RAS can cause hyperkalemia. Monitor serum electrolytes periodically.

Hydrochlorothiazide may alter glucose tolerance and raise serum levels of cholesterol and triglycerides.

Hyperuricemia may occur or frank gout may be precipitated in patients receiving thiazide therapy.

Hydrochlorothiazide decreases urinary calcium excretion and may cause elevations of serum calcium. Monitor calcium levels.

5.6 Acute Myopia and Secondary Angle-Closure Glaucoma

Hydrochlorothiazide, a sulfonamide, can cause an idiosyncratic reaction, resulting in acute transient myopia and acute angle-closure glaucoma. Symptoms include acute onset of decreased visual acuity or ocular pain and typically occur within hours to weeks of drug initiation. Untreated acute angle-closure glaucoma can lead to permanent vision loss. The primary treatment is to discontinue hydrochlorothiazide as rapidly as possible. Prompt medical or surgical treatments may need to be considered if the intraocular pressure remains uncontrolled. Risk factors for developing acute angle-closure glaucoma may include a history of sulfonamide or penicillin allergy.

5.7 Systemic Lupus Erythematosus

Thiazide diuretics have been reported to cause exacerbation or activation of systemic lupus erythematosus.

5.8 Sprue-Like Enteropathy

Severe, chronic diarrhea with substantial weight loss has been reported in patients taking olmesartan months to years after drug initiation. Intestinal biopsies of patients often demonstrated villous atrophy. If a patient develops these symptoms during treatment with olmesartan, exclude other etiologies. Consider discontinuation of olmesartan medoxomil and hydrochlorothiazide in cases where no other etiology is identified.

6 ADVERSE REACTIONS

The following adverse reactions with olmesartan medoxomil and hydrochlorothiazide are described elsewhere:

- Hypotension in Volume- or Salt-Depleted Patients [see Warnings and Precautions (5.2)]
- Impaired Renal Function [see Warnings and Precautions (5.3)]
- Hypersensitivity Reactions [see Warnings and Precautions (5.4)]
- Electrolyte and Metabolic Imbalances [see Warnings and Precautions (5.5)]
- Acute Myopia and Secondary Angle-Closure Glaucoma [see Warnings and Precautions (5.6)]
- Systemic Lupus Erythematosus [see Warnings and Precautions (5.7)]
- Sprue-Like Enteropathy [see Warnings and Precautions (5.8)]

6.1 Clinical Trials Experience

Because clinical studies are conducted under widely varying conditions, adverse reaction rates observed in the clinical studies of a drug cannot be directly compared to rates in the clinical studies of another drug and may not reflect the rates observed in practice.

Olmesartan medoxomilandhydrochlorothiazide

The concomitant use of olmesartan medoxomil and hydrochlorothiazide was evaluated for safety in 1243 hypertensive patients. Treatment with olmesartan medoxomil and hydrochlorothiazide was well tolerated, with an incidence of adverse events similar to that of placebo. Adverse reactions were generally mild, transient and not dependent on the dose of olmesartan medoxomil and hydrochlorothiazide.

The rate of withdrawals for adverse events in all trials of hypertensive patients was 2.0% (25/1243) on olmesartan medoxomil plus hydrochlorothiazide and 2.0% (7/342) on placebo.

In a placebo-controlled, factorial clinical trial of olmesartan medoxomil (2.5 mg to 40 mg) and hydrochlorothiazide (12.5 mg to 25 mg), the following adverse reactions reported in Table 1 occurred in >2% of patients, and more often on the olmesartan medoxomil and hydrochlorothiazide combination than on placebo.

Table 1: Adverse Reactions in a Factorial Trial of Patients with Hypertension
 | Olmesartan/HCTZ (N=247) (%) | Olmesartan (N=125) (%) | HCTZ (N=88) (%) | Placebo (N=42) (%)
Nausea | 3 | 2 | 1 | 0
Hyperuricemia | 4 | 0 | 2 | 2
Dizziness | 9 | 1 | 8 | 2
Upper Respiratory Infection | 7 | 6 | 7 | 0

Other adverse reactions that have been reported with an incidence of greater than 1.0%, whether or not attributed to treatment, in the more than 1200 hypertensive patients treated with olmesartan medoxomil and hydrochlorothiazide in controlled or open-label trials are listed below.

Body as a Whole:chest pain, back pain, peripheral edema
Central and Peripheral Nervous System:vertigo
Gastrointestinal:abdominal pain, dyspepsia, gastroenteritis, diarrhea
Liver and Biliary System:SGOT increased, GGT increased, ALT increased
Metabolic and Nutritional:creatine phosphokinase increased
Musculoskeletal:arthritis, arthralgia, myalgia
Respiratory System:coughing
Skin and Appendages Disorders:rash
Urinary System:hematuria

Facial edema was reported in 2/1243 patients receiving olmesartan medoxomil and hydrochlorothiazide. Angioedema has been reported with angiotensin II receptor antagonists, including olmesartan medoxomil and hydrochlorothiazide.

Hydrochlorothiazide

Other adverse reactions that have been reported with hydrochlorothiazide are listed below:

Body as a Whole:weakness
Digestive:pancreatitis, jaundice (intrahepatic cholestatic jaundice), sialadenitis, cramping, gastric irritation
Hematologic:aplastic anemia, agranulocytosis, leukopenia, hemolytic anemia, thrombocytopenia
Hypersensitivity:purpura, photosensitivity, urticaria, necrotizing angiitis (vasculitis and cutaneous vasculitis), fever, respiratory distress including pneumonitis and pulmonary edema, anaphylactic reactions
Metabolic:glycosuria, hyperuricemia
Musculoskeletal:muscle spasm
Nervous System/Psychiatric:restlessness
Renal:renal dysfunction, interstitial nephritis
Skin:erythema multiforme including Stevens-Johnson syndrome, exfoliative dermatitis including toxic epidermal necrolysis
Special Senses:transient blurred vision, xanthopsia

Clinical Laboratory Test Findings

Creatinine/bloodureanitrogen (BUN):Minor elevations in creatinine and BUN occurred in 1.7% and 2.5% respectively, of patients taking olmesartan medoxomil and hydrochlorothiazide and 0% and 0% respectively, given placebo in controlled clinical trials.

6.2 Post-marketing Experience

The following adverse reactions have been identified during post-approval use of olmesartan medoxomil and hydrochlorothiazide. Because these reactions are reported voluntarily from a population of uncertain size, it is not always possible to reliably estimate their frequency or establish a causal relationship to drug exposure:

Body as a Whole:Asthenia
Gastrointestinal:Vomiting
Metabolic:Hyperkalemia
Musculoskeletal:Rhabdomyolysis
Skin and Appendages:Alopecia, pruritus

Data from one controlled trial and an epidemiologic study have suggested that high-dose olmesartan may increase cardiovascular (CV) risk in diabetic patients, but the overall data are not conclusive. The randomized, placebo-controlled, double-blind ROADMAP trial (Randomized Olmesartan And Diabetes MicroAlbuminuria Prevention trial, n=4447) examined the use of olmesartan, 40 mg daily, vs. placebo in patients with type 2 diabetes mellitus, normoalbuminuria, and at least one additional risk factor for CV disease.

The trial met its primary endpoint, delayed onset of microalbuminuria, but olmesartan had no beneficial effect on decline in glomerular filtration rate (GFR). There was a finding of increased CV mortality (adjudicated sudden cardiac death, fatal myocardial infarction, fatal stroke, revascularization death) in the olmesartan group compared to the placebo group (15 olmesartan vs. 3 placebo, HR 4.9, 95% confidence interval [CI], 1.4, 17), but the risk of non-fatal myocardial infarction was lower with olmesartan (HR 0.64, 95% CI 0.35, 1.18).

The epidemiologic study included patients 65 years and older with overall exposure of > 300,000 patient-years. In the sub-group of diabetic patients receiving high-dose olmesartan (40 mg/d) for > 6 months, there appeared to be an increased risk of death (HR 2.0, 95% CI 1.1, 3.8) compared to similar patients taking other angiotensin receptor blockers. In contrast, high-dose olmesartan use in non-diabetic patients appeared to be associated with a decreased risk of death (HR 0.46, 95% CI 0.24, 0.86) compared to similar patients taking other angiotensin receptor blockers. No differences were observed between the groups receiving lower doses of olmesartan compared to other angiotensin blockers or those receiving therapy for < 6 months.

Overall, these data raise a concern of a possible increased CV risk associated with the use of high-dose olmesartan in diabetic patients. There are, however, concerns with the credibility of the finding of increased CV risk, notably the observation in the large epidemiologic study for a survival benefit in non-diabetics of a magnitude similar to the adverse finding in diabetics.

Non-melanoma Skin Cancer

Hydrochlorothiazide is associated with an increased risk of non-melanoma skin cancer. In a study conducted in the Sentinel System, increased risk was predominantly for squamous cell carcinoma (SCC) and in white patients taking large cumulative doses. The increased risk for SCC in the overall population was approximately 1 additional case per 16,000 patients per year, and for white patients taking a cumulative dose of ≥50,000mg the risk increase was approximately 1 additional SCC case for every 6,700 patients per year.

7 DRUG INTERACTIONS

7.1 Agents Increasing Serum Potassium

Coadministration of olmesartan medoxomil and hydrochlorothiazide with other drugs that raise serum potassium levels may result in hyperkalemia. Monitor serum potassium in such patients.

7.2 Lithium

Increases in serum lithium concentrations and lithium toxicity have been reported during concomitant administration of lithium with angiotensin II receptor antagonists or hydrochlorothiazide. Monitor serum lithium levels during concomitant use.

7.3 Non-Steroidal Anti-Inflammatory Agents including Selective Cyclooxygenase-2 Inhibitors (COX-2 Inhibitors)

Olmesartanmedoxomil

In patients who are elderly, volume-depleted (including those on diuretic therapy), or with compromised renal function, co-administration of NSAIDs, including selective COX-2 inhibitors, with angiotensin II receptor antagonists (including olmesartan medoxomil) may result in deterioration of renal function, including possible acute renal failure. These effects are usually reversible. Monitor renal function periodically in patients receiving olmesartan medoxomil and NSAID therapy.

The antihypertensive effect of angiotensin II receptor antagonists, including olmesartan medoxomil may be attenuated by NSAIDs including selective COX-2 inhibitors.

Hydrochlorothiazide

In some patients the administration of a NSAID can reduce the diuretic, natriuretic, and antihypertensive effects of thiazide diuretics. Therefore, monitor blood pressure closely.

7.4 Dual Blockade of the Renin Angiotensin System

Dual blockade of the RAS with angiotensin receptor blockers, ACE inhibitors, or aliskiren is associated with increased risks of hypotension, hyperkalemia, and changes in renal function (including acute renal failure) compared to monotherapy. Most patients receiving the combination of two RAS inhibitors do not obtain any additional benefit compared to monotherapy. In general, avoid combined use of RAS inhibitors. Closely monitor blood pressure, renal function and electrolytes in patients on olmesartan medoxomil and hydrochlorothiazide and other agents that affect the RAS.

Do not co-administer aliskiren with olmesartan medoxomil and hydrochlorothiazide in patients with diabetes [see Contraindications (4)].Avoid use of aliskiren with olmesartan medoxomil and hydrochlorothiazide in patients with renal impairment (GFR <60 ml/min).

7.5 Colesevelam Hydrochloride

Concurrent administration of bile acid sequestering agent colesevelam hydrochloride reduces the systemic exposure and peak plasma concentration of olmesartan. Administration of olmesartan at least 4 hours prior to colesevelam hydrochloride decreased the drug interaction effect. Consider administering olmesartan at least 4 hours before the colesevelam hydrochloride dose [see Clinical Pharmacology (12.3)].

7.6 The Use of Hydrochlorothiazidewith Other Drugs

When administered concurrently the following drugs may interact with thiazide diuretics:

Antidiabeticdrugs (oral agents and insulin):Dosage adjustment of the antidiabetic drug may be required.

Ion exchange resins:Staggering the dosage of hydrochlorothiazide and ion exchange resins (e.g., cholestyramine, colestipol) such that hydrochlorothiazide is administered at least 4 hours before or 4 – 6 hours after the administration of resins would potentially minimize the interaction [see Clinical Pharmacology (12.3)].

Corticosteroids, ACTH:Intensified electrolyte depletion, particularly hypokalemia.

8 USE IN SPECIFIC POPULATIONS

8.1 Pregnancy

Pregnancy Category D

Use of drugs that act on the renin-angiotensin system during the second and third trimesters of pregnancy reduces fetal renal function and increases fetal and neonatal morbidity, and death. Resulting oligohydramnios can be associated with fetal lung hypoplasia and skeletal deformations. Potential neonatal adverse effects include skull hypoplasia, anuria, hypotension, renal failure, and death. When pregnancy is detected, discontinue olmesartan medoxomil and hydrochlorothiazide as soon as possible. These adverse outcomes are usually associated with use of these drugs in the second and third trimester of pregnancy. Most epidemiologic studies examining fetal abnormalities after exposure to antihypertensive use in the first trimester have not distinguished drugs affecting the renin-angiotensin system from other antihypertensive agents. Appropriate management of maternal hypertension during pregnancy is important to optimize outcomes for both mother and fetus.

In the unusual case that there is no appropriate alternative to therapy with drugs affecting the renin-angiotensin system for a particular patient, apprise the mother of the potential risk to the fetus. Perform serial ultrasound examinations to assess the intraamniotic environment. If oligohydramnios is observed, discontinue olmesartan medoxomil and hydrochlorothiazide, unless it is considered lifesaving for the mother. Fetal testing may be appropriate, based on the week of pregnancy. Patients and physicians should be aware, however, that oligohydramnios may not appear until after the fetus has sustained irreversible injury. Closely observe infants with histories of in utero exposure to olmesartan medoxomil and hydrochlorothiazide for hypotension, oliguria, and hyperkalemia [see Use in Specific Populations (8.4)].

8.3 Nursing Mothers

It is not known whether olmesartan is excreted in human milk, but olmesartan is secreted at low concentration in the milk of lactating rats. Thiazides appear in human milk. Because of the potential for adverse effects on the nursing infant, a decision should be made whether to discontinue nursing or discontinue volmesartan medoxomil and hydrochlorothiazide, taking into account the importance of the drug to the mother.

8.4 Pediatric Use

Neonates with a history of in utero exposure to olmesartan medoxomil and hydrochlorothiazide:

If oliguria or hypotension occurs, direct attention toward support of blood pressure and renal perfusion. Exchange transfusions or dialysis may be required as a means of reversing hypotension and substituting for disordered renal function.

Safety and effectiveness of olmesartan medoxomil and hydrochlorothiazide in pediatric patients have not been established.

8.5 Geriatric Use

Clinical studies of olmesartan medoxomil and hydrochlorothiazide did not include sufficient numbers of subjects aged 65 and over to determine whether they respond differently from younger subjects. Other reported clinical experience has not identified differences in responses between the elderly and younger patients. In general, dose selection for an elderly patient should be cautious, usually starting at the low end of the dosing range, reflecting the greater frequency of decreased hepatic, renal or cardiac function and of concomitant diseases or other drug therapy.

Olmesartan and hydrochlorothiazide are substantially excreted by the kidney, and the risk of toxic reactions to olmesartan medoxomil and hydrochlorothiazide may be greater in patients with impaired renal function.

8.6 Renal Impairment

Safety and effectiveness of olmesartan medoxomil and hydrochlorothiazide in patients with severe renal impairment (CrCl ≤ 30 mL/min) have not been established. No dose adjustment is required in patients with mild (CrCl 60-90 mL/min) or moderate (CrCl 30-60) renal impairment.

8.7 Hepatic Impairment

Olmesartanmedoxomil

No dose adjustment is necessary for patients with mild-to-severe liver disease.

Hydrochlorothiazide

Minor alterations of fluid and electrolyte balance may precipitate hepatic coma in patients with impaired hepatic function or progressive liver disease.

10 OVERDOSAGE

Olmesartan medoxomil

Limited data are available related to overdosage of olmesartan medoxomil in humans. The most likely manifestations of overdosage would be hypotension and tachycardia; bradycardia could be encountered if parasympathetic (vagal) stimulation occurs. If symptomatic hypotension should occur, supportive treatment should be initiated. The dialyzability of olmesartan is unknown.

No lethality was observed in acute toxicity studies in mice and rats given single oral doses up to 2000 mg/kg olmesartan medoxomil. The minimum lethal oral dose of olmesartan medoxomil in dogs was greater than 1500 mg/kg.

Hydrochlorothiazide

The most common signs and symptoms of hydrochlorothiazide overdose observed in humans are those caused by electrolyte depletion (hypokalemia, hypochloremia, hyponatremia) and dehydration resulting from excessive diuresis. If digitalis has also been administered, hypokalemia may accentuate cardiac arrhythmias. The degree to which hydrochlorothiazide is removed by hemodialysis has not been established. The oral LD50of hydrochlorothiazide is greater than 10 g/kg in both mice and rats.

11 DESCRIPTION

Olmesartan medoxomil and hydrochlorothiazide is a combination of an angiotensin II receptor antagonist (AT1subtype), olmesartan medoxomil, and a thiazide diuretic, hydrochlorothiazide (HCTZ).

Olmesartan medoxomil is 2,3-dihydroxy-2-butenyl 4-(1-hydroxy-1-methylethyl)-2-propyl-1-[ p-(o-1 H-tetrazol-5-ylphenyl)benzyl]imidazole-5-carboxylate, cyclic 2,3-carbonate.

Its empirical formula is C29H30N6O6and its structural formula is:

Olmesartan medoxomil is a white to light yellowish-white powder or crystalline powder with a molecular weight of 558.6. It is practically insoluble in water and sparingly soluble in methanol.

Hydrochlorothiazide is 6-chloro-3,4-dihydro-2 H-1,2,4-benzo-thiadiazine-7-sulfonamide 1,1-dioxide. Its empirical formula is C7H8ClN3O4S2and its structural formula is:

Hydrochlorothiazide is a white, or practically white, crystalline powder with a molecular weight of 297.7. Hydrochlorothiazide is slightly soluble in water but freely soluble in sodium hydroxide solution.

Olmesartan medoxomil and hydrochlorothiazide is available for oral administration in tablets containing 20 mg or 40 mg of olmesartan medoxomil combined with 12.5 mg of hydrochlorothiazide, or 40 mg of olmesartan medoxomil combined with 25 mg of hydrochlorothiazide. Inactive ingredients include: hydroxypropylcellulose, hypromellose, lactose monohydrate, low-substituted hydroxypropylcellulose, magnesium stearate, microcrystalline cellulose, red iron oxide, talc, titanium dioxide and yellow iron oxide.

12 CLINICAL PHARMACOLOGY

12.1 Mechanism of Action

Olmesartan medoxomil

Angiotensin II is formed from angiotensin I in a reaction catalyzed by angiotensin converting enzyme (ACE, kininase II). Angiotensin II is the principal pressor agent of the renin-angiotensin system, with effects that include vasoconstriction, stimulation of synthesis and release of aldosterone, cardiac stimulation and renal reabsorption of sodium. Olmesartan blocks the vasoconstrictor effects of angiotensin II by selectively blocking the binding of angiotensin II to the AT1receptor in vascular smooth muscle. Its action is, therefore, independent of the pathways for angiotensin II synthesis.

An AT2receptor is found also in many tissues, but this receptor is not known to be associated with cardiovascular homeostasis. Olmesartan has more than a 12,500-fold greater affinity for the AT1receptor than for the AT2receptor.

Blockade of the angiotensin II receptor inhibits the negative regulatory feedback of angiotensin II on renin secretion, but the resulting increased plasma renin activity and circulating angiotensin II levels do not overcome the effect of olmesartan on blood pressure.

Hydrochlorothiazide

Hydrochlorothiazide is a thiazide diuretic. Thiazides affect the renal tubular mechanisms of electrolyte reabsorption, directly increasing excretion of sodium and chloride in approximately equivalent amounts. Indirectly, the diuretic action of hydrochlorothiazide reduces plasma volume, with consequent increases in plasma renin activity, increases in aldosterone secretion, increases in urinary potassium loss, and decreases in serum potassium. The renin-aldosterone link is mediated by angiotensin II, so co-administration of an angiotensin II receptor antagonist tends to reverse the potassium loss associated with these diuretics. The mechanism of the antihypertensive effect of thiazides is not fully understood.

12.2 Pharmacodynamics

Olmesartan medoxomil

Olmesartan medoxomil doses of 2.5 to 40 mg inhibit the pressor effects of angiotensin I infusion. The duration of the inhibitory effect was related to dose, with doses of olmesartan medoxomil >40 mg giving >90% inhibition at 24 hours.

Plasma concentrations of angiotensin I and angiotensin II and plasma renin activity (PRA) increase after single and repeated administration of olmesartan medoxomil to healthy subjects and hypertensive patients. Repeated administration of up to 80 mg olmesartan medoxomil had minimal influence on aldosterone levels and no effect on serum potassium.

Hydrochlorothiazide

After oral administration of hydrochlorothiazide, diuresis begins within 2 hours, peaks in about 4 hours and lasts about 6 to 12 hours.

Drug Interactions

Hydrochlorothiazide

Alcohol, barbiturates, or narcotics:Potentiation of orthostatic hypotension may occur.

Skeletalmusclerelaxants, non-depolarizing (e.g., tubocurarine):Increased responsiveness to the muscle relaxant may occur.

Digitalis glycosides:Thiazide-induced hypokalemia or hypomagnesemia may predispose to digoxin toxicity.

12.3 Pharmacokinetics

Absorption

Olmesartan: Olmesartan medoxomil is completely bioactivated by ester hydrolysis to olmesartan during absorption from the gastrointestinal tract. The absolute bioavailability of olmesartan is approximately 26%. After oral administration, the peak plasma concentration (Cmax) of olmesartan is reached after 1 to 2 hours. Food does not affect the bioavailability of olmesartan.

Olmesartan shows linear pharmacokinetics following single oral doses of up to 320 mg and multiple oral doses of up to 80 mg. Steady-state levels of olmesartan are achieved within 3 to 5 days and no accumulation in plasma occurs with once-daily dosing.

Hydrochlorothiazide: The estimated absolute bioavailability of hydrochlorothiazide after oral administration is about 70%. Peak plasma hydrochlorothiazide concentrations (Cmax) are reached within 2 to 5 hours after oral administration. There is no clinically significant effect of food on the bioavailability of hydrochlorothiazide.

The pharmacokinetics of hydrochlorothiazide is dose proportional in the range of 12.5 to 75 mg.

Distribution

Olmesartan: The volume of distribution of olmesartan is approximately 17 L. Olmesartan is highly bound to plasma proteins (99%) and does not penetrate red blood cells. The protein binding is constant at plasma olmesartan concentrations well above the range achieved with recommended doses.

In rats, olmesartan crossed the blood-brain barrier poorly, if at all. Olmesartan passed across the placental barrier in rats and was distributed to the fetus. Olmesartan was distributed to milk at low levels in rats.

Hydrochlorothiazide: Hydrochlorothiazide binds to albumin (40 to 70%) and distributes into erythrocytes. Following oral administration, plasma hydrochlorothiazide concentrations decline bi-exponentially, with a mean distribution half-life of about 2 hours and an elimination half-life of about 10 hours.

Hydrochlorothiazide crosses the placental but not the blood-brain barrier and is excreted in breast milk.

Metabolism

Olmesartan:Olmesartan does not undergo further metabolism.

Hydrochlorothiazide: Hydrochlorothiazide is not metabolized.

Elimination

Olmesartan: Olmesartan appears to be eliminated in a biphasic manner with a terminal elimination half-life of approximately 13 hours. Total plasma clearance of olmesartan is 1.3 L/h, with a renal clearance of 0.6 L/h. Approximately 35% to 50% of the absorbed dose is recovered in urine while the remainder is eliminated in feces via the bile.

Hydrochlorothiazide: About 70% of an orally administered dose of hydrochlorothiazide is eliminated in the urine as unchanged drug.

Specific populations

Olmesartanmedoxomil

Pediatric:The pharmacokinetics of olmesartan were studied in pediatric hypertensive patients aged 1 to16 years. The clearance of olmesartan in pediatric patients was similar to that in adult patients when adjusted by the body weight. Olmesartan pharmacokinetics have not been investigated in pediatric patients less than 1 year of age.

Geriatric:The pharmacokinetics of olmesartan were studied in the elderly (≥65 years). Overall, maximum plasma concentrations of olmesartan were similar in young adults and the elderly. Modest accumulation of olmesartan was observed in the elderly with repeated dosing; AUCss,τwas 33% higher in elderly patients, corresponding to an approximate 30% reduction in CLR.

Gender:Minor differences were observed in the pharmacokinetics of olmesartan in women compared to men. AUC and Cmaxwere 10-15% higher in women than in men.

Renalinsufficiency:In patients with renal insufficiency, serum concentrations of olmesartan were elevated compared to subjects with normal renal function. After repeated dosing, the AUC was approximately tripled in patients with severe renal impairment (creatinine clearance <20 mL/min). The pharmacokinetics of olmesartan in patients undergoing hemodialysis has not been studied.

Hepaticinsufficiency:Increases in AUC0-∞and Cmaxfor olmesartan were observed in patients with moderate hepatic impairment compared to those in matched controls, with an increase in AUC of about 60%.

Hydrochlorothiazide

Renalinsufficiency:In a study in individuals with impaired renal function, the mean elimination half-life of hydrochlorothiazide doubled in individuals with mild/moderate renal impairment (30 < CrCl < 90 mL/min) and tripled in severe renal impairment (≤ 30 mL/min), when compared to individuals with normal renal function (CrCl > 90 mL/min).

Drug Interactions

Olmesartan

No significant drug interactions were reported in studies in which olmesartan medoxomil was co-administered with digoxin or warfarin in healthy volunteers.

The bioavailability of olmesartan medoxomil was not significantly altered by the co-administration of antacids [Al(OH)3/Mg(OH)2].

Olmesartan medoxomil is not metabolized by the cytochrome P450 system and has no effects on P450 enzymes; thus, interactions with drugs that inhibit, induce, or are metabolized by those enzymes are not expected.

Bile acid sequestering agent colesevelam

Concomitant administration of 40 mg olmesartan medoxomil and 3750 mg colesevelam hydrochloride in healthy subjects resulted in 28% reduction in Cmax and 39% reduction in AUC of olmesartan. Lesser effects, 4% and 15% reduction in Cmax and AUC respectively, were observed when olmesartan medoxomil was administered 4 hours prior to colesevelam hydrochloride [see Drug Interactions (7.5)].

Hydrochlorothiazide

Drugs that alter gastrointestinal motility:The bioavailability of thiazide-type diuretics may be increased by anticholinergic agents (e.g. atropine, biperiden), apparently due to a decrease in gastrointestinal motility and the stomach emptying rate. Conversely, pro-kinetic drugs may decrease the bioavailability of thiazide diuretics.

Cholestyramine:In a dedicated drug interaction study, administration of cholestyramine 2 h before hydrochlorothiazide resulted in a 70% reduction in exposure to hydrochlorothiazide. Further, administration of hydrochlorothiazide 2 h before cholestyramine, resulted in 35% reduction in exposure to hydrochlorothiazide.

Lithium:Diuretic agents reduce the renal clearance of lithium and increase the risk of lithium toxicity [see Drug Interactions (7.2)].

Antineoplastic agents (e.g. cyclophosphamide, methotrexate):Concomitant use of thiazide diuretics may reduce renal excretion of cytotoxic agents and enhance their myelosuppressive effects.

13 NONCLINICAL TOXICOLOGY

13.1 Carcinogenesis, Mutagenesis, Impairment of Fertility

Olmesartan medoxomilandhydrochlorothiazide

No carcinogenicity studies with olmesartan medoxomil and hydrochlorothiazide have been conducted.

Olmesartan medoxomil and hydrochlorothiazide in a ratio of 20:12.5 were negative in the Salmonella-Escherichia coli/mammalian microsome reverse mutation test up to the maximum recommended plate concentration for the standard assays. Olmesartan medoxomil and hydrochlorothiazide were tested individually and in combination ratios of 40:12.5, 20:12.5 and 10:12.5, for clastogenic activity in the in vitroChinese hamster lung (CHL) chromosomal aberration assay. A positive response was seen for each component and combination ratio. However, no synergism in clastogenic activity was detected between olmesartan medoxomil and hydrochlorothiazide at any combination ratio. Olmesartan medoxomil and hydrochlorothiazide in a ratio of 20:12.5, administered orally, tested negative in the in vivomouse bone marrow erythrocyte micronucleus assay at administered doses of up to 3144 mg/kg.

No studies of impairment of fertility with olmesartan medoxomil and hydrochlorothiazide have been conducted.

Olmesartan medoxomil

Olmesartan medoxomil was not carcinogenic when administered by dietary administration to rats for up to 2 years. The highest dose tested (2000 mg/kg/day) was, on a mg/m^2basis, about 480 times the maximum recommended human dose (MRHD) of 40 mg/day. Two carcinogenicity studies conducted in mice, a 6-month gavage study in the p53 knockout mouse and a 6-month dietary administration study in the Hras2 transgenic mouse, at doses of up to 1000 mg/kg/day (about 120 times the MRHD), revealed no evidence of a carcinogenic effect of olmesartan medoxomil.

Both olmesartan medoxomil and olmesartan tested negative in the in vitroSyrian hamster embryo cell transformation assay and showed no evidence of genetic toxicity in the Ames (bacterial mutagenicity) test. However, both were shown to induce chromosomal aberrations in cultured cells in vitro(Chinese hamster lung) and both tested positive for thymidine kinase mutations in the in vitromouse lymphoma assay. Olmesartan medoxomil tested negative in vivofor mutations in the MutaMouse intestine and kidney, and for clastogenicity in mouse bone marrow (micronucleus test) at oral doses of up to 2000 mg/kg (olmesartan not tested).

Fertility of rats was unaffected by administration of olmesartan medoxomil at dose levels as high as 1000 mg/kg/day (240 times the MRHD) in a study in which dosing was begun 2 (female) or 9 (male) weeks prior to mating.

Hydrochlorothiazide

Two-year feeding studies in mice and rats conducted under the auspices of the National Toxicology Program (NTP) uncovered no evidence of a carcinogenic potential of hydrochlorothiazide in female mice (at doses of up to approximately 600 mg/kg/day) or in male and female rats (at doses of up to approximately 100 mg/kg/day). The NTP, however, found equivocal evidence for hepatocarcinogenicity in male mice.

Hydrochlorothiazide was not genotoxic in vitroin the Ames mutagenicity assay of Salmonella typhimuriumstrains TA 98, TA 100, TA 1535, TA 1537 and TA 1538, or in the Chinese Hamster Ovary (CHO) test for chromosomal aberrations. It was also not genotoxic in vivoin assays using mouse germinal cell chromosomes, Chinese hamster bone marrow chromosomes, or the Drosophilasex-linked recessive lethal trait gene. Positive test results were obtained in the in vitroCHO Sister Chromatid Exchange (clastogenicity) assay, the Mouse Lymphoma Cell (mutagenicity) assay and the Aspergillus nidulansnon-disjunction assay.

Hydrochlorothiazide had no adverse effects on the fertility of mice and rats of either sex in studies wherein these species were exposed, via their diet, to doses of up to 100 and 4 mg/kg, respectively, prior to mating and throughout gestation.

13.3 Developmental Toxicity

Olmesartanmedoxomiland hydrochlorothiazide

No teratogenic effects were observed when 1.6:1 combinations of olmesartan medoxomil and hydrochlorothiazide were administered to pregnant mice at oral doses up to 1625 mg/kg/day (122 times the maximum recommended human dose [MRHD] on a mg/m^2basis) or pregnant rats at oral doses up to 1625 mg/kg/day (280 times the MRHD on a mg/m^2basis). In rats, however, fetal body weights at 1625 mg/kg/day (a toxic, sometimes lethal dose in the dams) were significantly lower than control. The no observed effect dose for developmental toxicity in rats, 162.5 mg/kg/day, is about 28 times, on a mg/m^2basis, the MRHD of olmesartan medoxomil and hydrochlorothiazide (40 mg olmesartan medoxomil /25 mg hydrochlorothiazide/day).

14 CLINICAL STUDIES

Olmesartan medoxomilandhydrochlorothiazide

In clinical trials 1230 patients were exposed to the combination of olmesartan medoxomil (2.5 mg to 40 mg) and hydrochlorothiazide (12.5 mg to 25 mg). These trials included one placebo-controlled factorial trial in mild-moderate hypertensive patients (n=502) with combinations of olmesartan medoxomil (10 mg, 20 mg, 40 mg, or placebo) and hydrochlorothiazide (12.5 mg, 25 mg, or placebo). The antihypertensive effect of the combination on trough blood pressure was related to the dose of each component (see Table 2).

Once-daily dosing with 20 mg olmesartan medoxomil and 12.5 mg hydrochlorothiazide, 40 mg olmesartan medoxomil and 12.5 mg hydrochlorothiazide or 40 mg olmesartan medoxomil and 25 mg hydrochlorothiazide produced mean placebo-adjusted blood pressure reductions at trough (24 hours post-dosing) ranging from 17/8 to 24/14 mm Hg.

Table 2: Placebo-Adjusted Reductions in Sitting Systolic/Diastolic Blood Pressure (mmHg)
 | Olmesartan Medoxomil
HCTZ | 0 mg | 10 mg | 20 mg | 40 mg
0 mg | -- | 7/5 | 12/5 | 13/7
12.5 mg | 5/1 | 17/8 | 17/8 | 16/10
25 mg | 14/5 | 19/11 | 22/11 | 24/14

The antihypertensive effect had onset within 1 week and was near maximal at 4 weeks. The antihypertensive effect was independent of gender, but there were too few subjects to identify response differences based on race or age greater than or less than 65 years. No appreciable changes in trough heart rate were observed with combination therapy.

There are no trials of olmesartan medoxomil and hydrochlorothiazide demonstrating reductions in cardiovascular risk in patients with hypertension, but at least one drug pharmacologically similar to olmesartan medoxomil has demonstrated such benefits, and hydrochlorothiazide demonstrated reduction of cardiovascular risk in patients with hypertension.

Olmesartan medoxomil

The antihypertensive effects of olmesartan medoxomil have been demonstrated in seven placebo-controlled studies at doses ranging from 2.5 to 80 mg for 6 to 12 weeks, each showing statistically significant reductions in peak and trough blood pressure. A total of 2693 patients (2145 olmesartan medoxomil; 548 placebo) with essential hypertension were studied. Olmesartan medoxomil once daily (QD) lowered diastolic and systolic blood pressure. The response was dose-related. An olmesartan medoxomil dose of 20 mg daily produced a trough sitting BP reduction over placebo of about 10/6 mm Hg and a dose of 40 mg daily produced a trough sitting BP reduction over placebo of about 12/7 mm Hg. Olmesartan medoxomil doses greater than 40 mg had little additional effect. The onset of the antihypertensive effect occurred within 1 week and was largely manifest after 2 weeks.

The blood pressure lowering effect was maintained throughout the 24-hour period with olmesartan medoxomil once daily, with trough-to-peak ratios for systolic and diastolic response between 60 and 80%.

The blood pressure lowering effect of olmesartan medoxomil, with and without hydrochlorothiazide, was maintained in patients treated for up to 1 year. There was no evidence of tachyphylaxis during long-term treatment with olmesartan medoxomil or rebound effect following abrupt withdrawal of olmesartan medoxomil after 1 year of treatment.

The antihypertensive effect of olmesartan medoxomil was similar in men and women and in patients older and younger than 65 years. The effect was smaller in black patients (usually a low-renin population), as has been seen with other ACE inhibitors, angiotensin receptor blockers, and beta-blockers. Olmesartan medoxomil had an additional blood pressure lowering effect when added to hydrochlorothiazide.

16 HOW SUPPLIED/STORAGE AND HANDLING

Olmesartan medoxomil and hydrochlorothiazide is supplied as follows:

Olm/HCTZ | Shape | Color | Debossing
 |  |  | Side 1 | Side 2
20/12.5 mg | Round | Reddish-yellow | Sankyo | C22
40/12.5 mg | Oval | Reddish-yellow | Sankyo | C23
40/25 mg | Oval | Pink | Sankyo | C25

Tablets are packaged as follows:

 | 20/12.5 mg | 40/12.5 mg | 40/25 mg
Bottle of 90 tablets | 42291-924-90 | 42291-925-90 | 42291-926-90

Storage

Store at 20-25ºC (68-77ºF) [See USP Controlled Room Temperature].

17 PATIENT COUNSELING INFORMATION

Pregnancy:Advisefemale patients of childbearing age about the consequences of exposure to olmesartan medoxomil and hydrochlorothiazide during pregnancy. Discuss treatment options with women planning to become pregnant. Tell patients to report pregnancies to their physicians as soon as possible [see Use in Specific Populations (8.1)].

Symptomatichypotensionandsyncope:Advise patients that lightheadedness can occur, especially during the first days of therapy, and to report this symptom to a healthcare provider. Inform patients that dehydration from inadequate fluid intake, excessive perspiration, vomiting, or diarrhea may lead to an excessive fall in blood pressure. If syncope occurs advise patients, to contact their healthcare provider.

Potassium Supplements: Advise patients not to use potassium supplements or salt substitutes containing potassium without consulting their healthcare provider.

Acutemyopia andsecondaryangle-closureglaucoma:Advise patients to discontinue olmesartan medoxomil and hydrochlorothiazide and seek immediate medical attention if they experience symptoms of acute myopia or secondary angle-closure glaucoma [see Warnings and Precautions (5.6)].

Non-melanoma Skin Cancer:Instruct patients taking hydrochlorothiazide to protect skin from the sun and undergo regular skin cancer screening.

Manufactured for:

AvKARE

Pulaski, TN 38478

Mfg. Iss. 02/22

AV 07/23 (M)